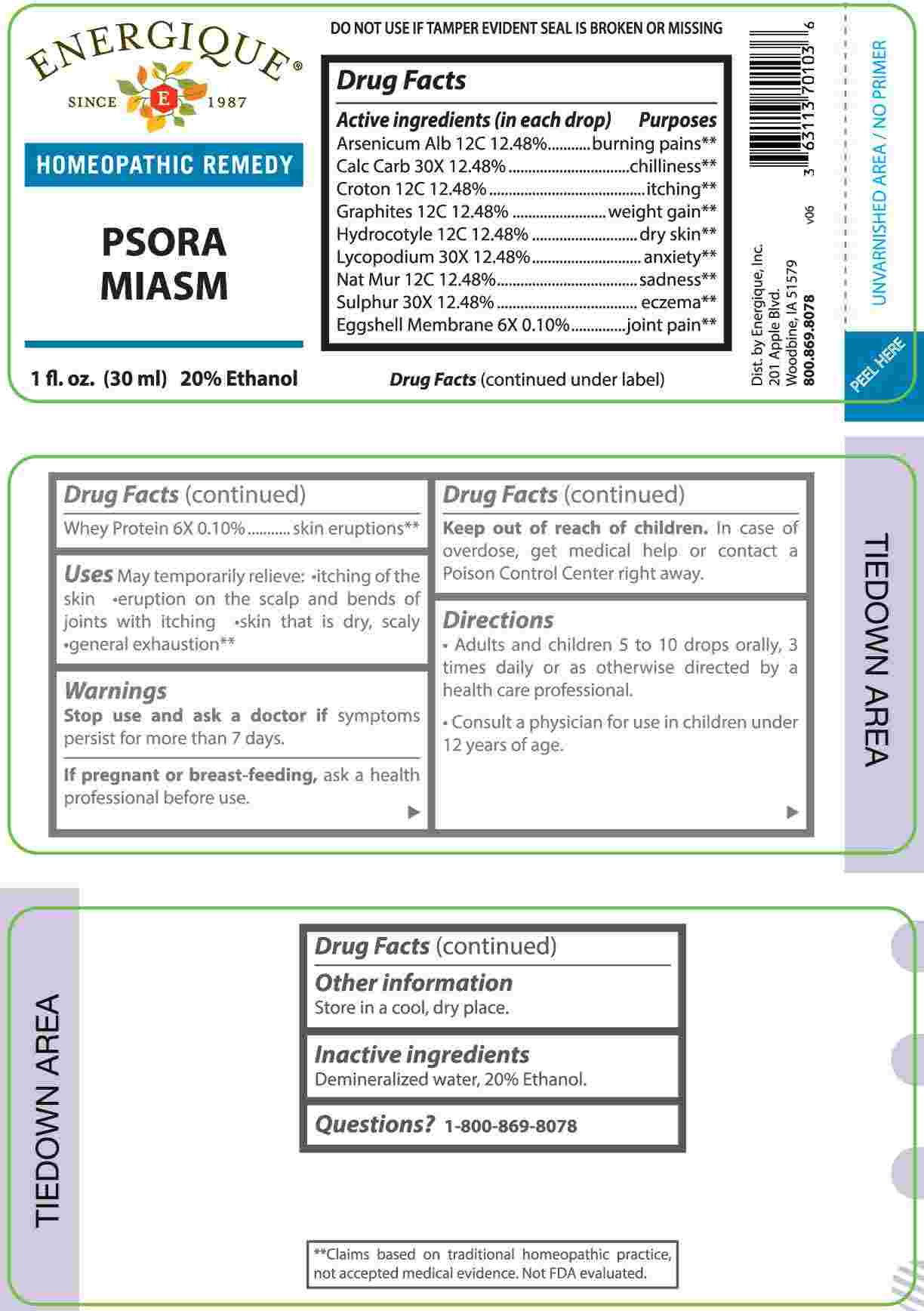 DRUG LABEL: Psora Miasm
NDC: 44911-0733 | Form: LIQUID
Manufacturer: Energique, Inc.
Category: homeopathic | Type: HUMAN OTC DRUG LABEL
Date: 20250313

ACTIVE INGREDIENTS: EGG SHELL MEMBRANE 6 [hp_X]/1 mL; WHEY 6 [hp_X]/1 mL; OYSTER SHELL CALCIUM CARBONATE, CRUDE 30 [hp_X]/1 mL; LYCOPODIUM CLAVATUM SPORE 30 [hp_X]/1 mL; SULFUR 30 [hp_X]/1 mL; ARSENIC TRIOXIDE 12 [hp_C]/1 mL; CROTON TIGLIUM SEED 12 [hp_C]/1 mL; GRAPHITE 12 [hp_C]/1 mL; CENTELLA ASIATICA WHOLE 12 [hp_C]/1 mL; SODIUM CHLORIDE 12 [hp_C]/1 mL
INACTIVE INGREDIENTS: WATER; ALCOHOL

DRUG FACTS:

ACTIVE INGREDIENTS:

(in each drop) Arsenicum Album 12C 12.48%, Calcarea Carbonica 30X 12.48%, Croton Tiglium 12C 12.48%, Graphites 12C 12.48%, Hydrocotyle Asiatica 12C 12.48%, Lycopodium Clavatum 30X 12.48%, Natrum Muriaticum 12C 12.48%, Sulphur 30X 12.48%, Eggshell Membrane 6X 0.10%, Whey Protein 6X 0.10%.

PURPOSE:

Arsenicum Album – burning pains,** Calcarea Carbonica - chilliness,** Croton Tiglium - itching,** Graphites – weight gain,** Hydrocotyle Asiatica – dry skin,** Lycopodium Clavatum - anxiety,** Natrum Muriaticum - sadness,** Sulphur - eczema,** Eggshell Membrane – joint pain,** Whey Protein – skin eruptions**

**Claims based on traditional homeopathic practice, not accepted medical evidence. Not FDA evaluated.

USES:

May temporarily relieve:

• itching of the skin • eruption on the scalp and bends of joints with itching

• skin that is dry, scaly • general exhaustion.**

**Claims based on traditional homeopathic practice, not accepted medical evidence. Not FDA evaluated.

WARNINGS:

Stop use and ask a doctor if symptoms persist for more than 7 days.

If pregnant or breast-feeding, ask a health professional before use.

Keep out of reach of children. In case of overdose, get medical help or contact a Poison Control Center right away.

DO NOT USE IF TAMPER EVIDENT SEAL IS BROKEN OR MISSING

Store in a cool, dry place.

KEEP OUT OF REACH OF CHILDREN:

In case of overdose, get medical help or contact a Poison Control Center right away.

DIRECTIONS:

• Adults and children 5 to 10 drops orally, 3 times daily or as otherwise directed by a health care professional.

• Consult a physician for use in children under 12 years of age.

INACTIVE INGREDIENTS:

Demineralized water, 20% ethanol.

QUESTIONS:

Dist. by Energique, Inc.

201 Apple Blvd.

Woodbine, IA 51579

800.869.8078

PACKAGE LABEL DISPLAY:

ENERGIQUE

SINCE 1987

HOMEOPATHIC REMEDY

PSORA MIASM

1 fl. oz. (30 ml)